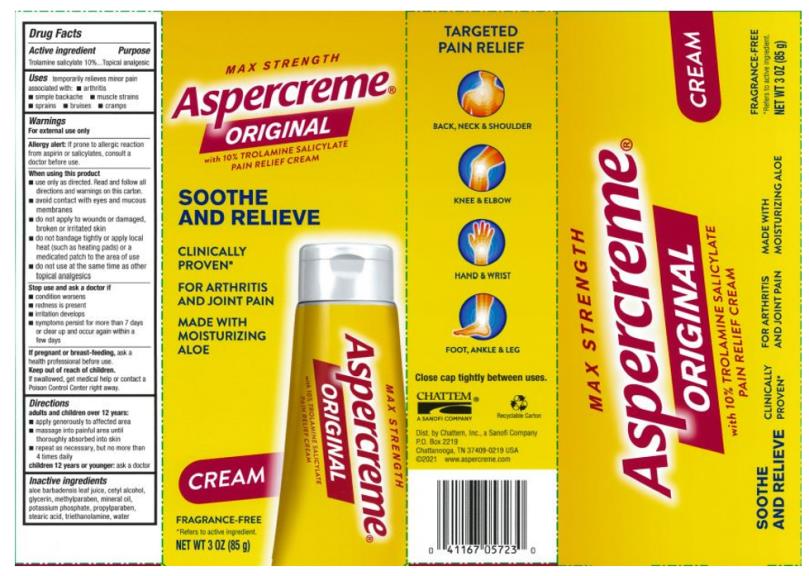 DRUG LABEL: Aspercreme Pain Relieving
NDC: 41167-0570 | Form: CREAM
Manufacturer: Chattem, Inc.
Category: otc | Type: HUMAN OTC DRUG LABEL
Date: 20240219

ACTIVE INGREDIENTS: TROLAMINE SALICYLATE 10 g/100 g
INACTIVE INGREDIENTS: ALOE VERA LEAF; CETYL ALCOHOL; GLYCERIN; METHYLPARABEN; MINERAL OIL; POTASSIUM PHOSPHATE, UNSPECIFIED FORM; PROPYLPARABEN; STEARIC ACID; TROLAMINE; WATER

Aspercreme Pain Relieving Creme

ASPERCEME® Pain Relieving Creme

Drug Facts

Active ingredient

Trolamine salicylate 10%

Purpose

Topical analgesic

Uses

temporary relieves minor pain associated with:

- arthritis
- simple backache
- muscle strains
- sprains
- bruises
- cramps

Warnings

For external use only

Allergy alert:

If prone to allergic reaction from aspirin or salicylates, consult a doctor before use.

When using this product

- use only as directed. Read and follow all directions and warnings on this label.
- do not bandage tightly or apply local heat (such as heating pads) to the area of use
- avoid contact with eyes or mucous membranes
- do not apply to wounds or damaged, broken or irritated skin
- do not use at the same time as other topical analgesics

Stop use and ask a doctor if

- condition worsens
- symptoms persist for more than 7 days or clear up and occur again within a few days
- redness is present
- irritation develops

If pregnant or breast-feeding,

ask a health professional before use.

Keep out of reach of children.

If swallowed, get medical help or contact a Poison Control Center right away.

Directions

adults and children over 12 years:

- apply generously to affected area
- massage into painful area until thoroughly absorbed into skin
- repeat as necessary, but no more than 3 to 4 times daily

children 12 years and younger: ask a doctor

Inactive ingredients

aloe barbadensis leaf juice, cetyl alcohol, glycerin, methylparaban, mineral oil, potassium phosphate, propylparaban, stearic acid, triethanolamine, water

Close cap tightly after use.

PRINCIPAL DISPLAY PANEL

MAX STRENGTH
Aspercreme®
ORIGINAL
with 10% Trolamine Salicylate
PAIN RELIEF CREAM
NET WT 3 oz (85 g)